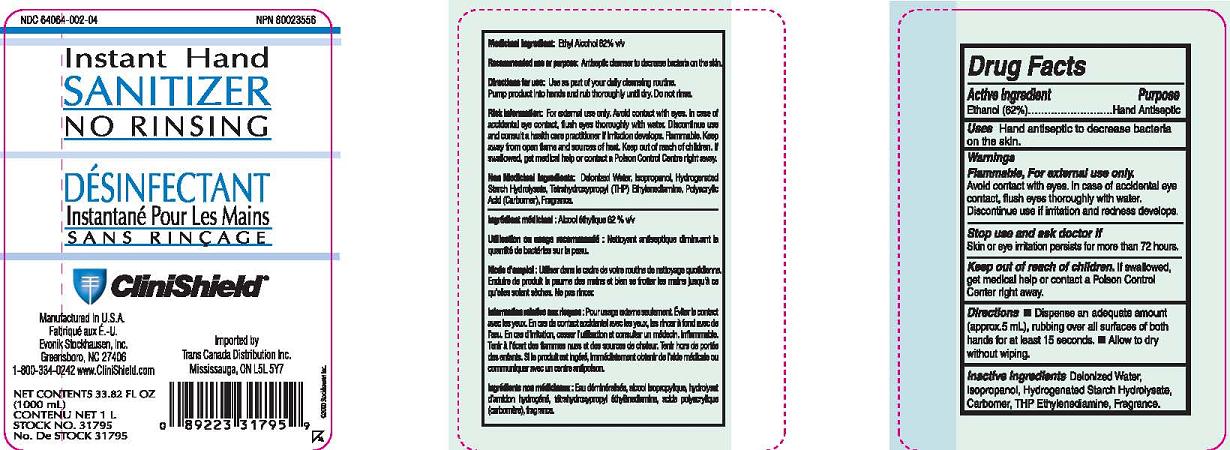 DRUG LABEL: Instant Hand Sanitizer
NDC: 64064-002 | Form: LIQUID
Manufacturer: Evonik Stockhausen, LLC
Category: otc | Type: HUMAN OTC DRUG LABEL
Date: 20111111

ACTIVE INGREDIENTS: Alcohol 62 mL/100 mL
INACTIVE INGREDIENTS: Water; Isopropyl Alcohol; Edetol; Carbomer Homopolymer Type C

Drug Facts

Active Ingredient

Ethanol (62%)

Purpose

Hand Antiseptic

Uses

Hand antiseptic to decrease bacteria on the skin.

Warnings

Flammable, For external use only.

Avoid contact with eyes. In case of accidental eye contact, flush eyes thoroughly with water.

Discontinue use if irritation and redness develops.

Stop use and ask doctor if

Skin or eye irritation persists for more than 72 hours

Keep out of reach of children.

If swallowed, get medical help or contact a Poison Control Center right away.

Directions

- Dispense an adequate amount (approx. 5 mL), rubbing all surfaces of both hands for at least 15 seconds.
- Allow to dry without wiping.

Inactive Ingredients

Deionized Water, Isopropanol, Hydrogenated Starch Hydrolysate, Carbomer, THP Ethylendiamine, Fragrance

Principal Display Panel

NDC 64064-002-04

Instant Hand

Sanitizer

No Rinsing

Desinfectant

Instantane Pour Les Mains

Sans Rincage

Clinishield

Manufactured in U.S.A.

Fabrique Aux E.-U.

Evonik Stockhausen, LLC

Greensboro, NC 27406

1-800-334-0242 www.CliniShield.com

Imported by

Trans Canada Distribution Inc.

Mississauga, ON L5L 5Y7

Net Contents 32.82 Fl Oz

(1000 mL)

Contenu Net 1 L

Stock No. 31795

No. De Stock 31795